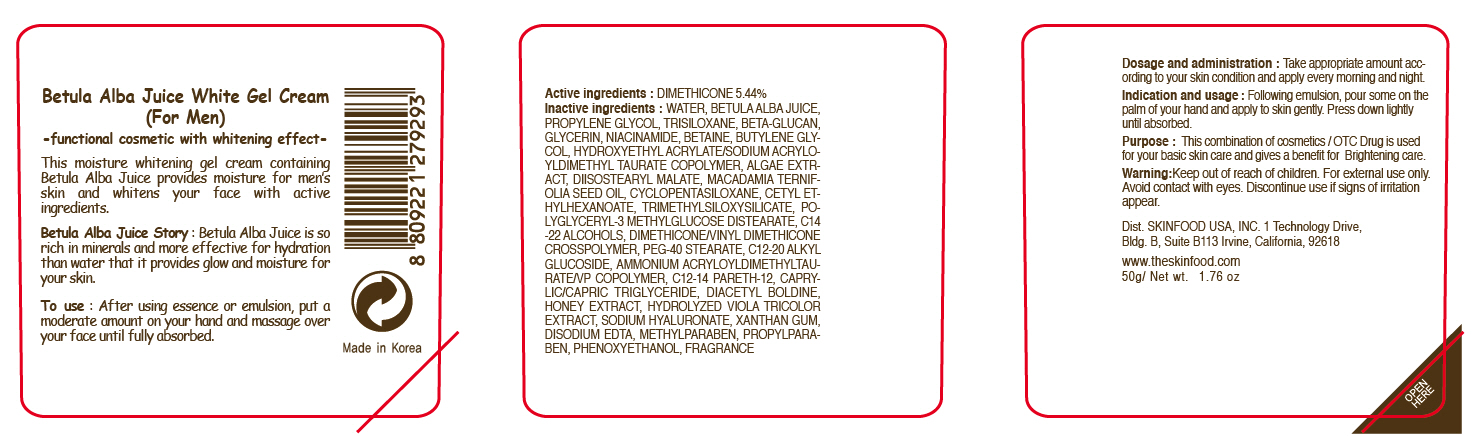 DRUG LABEL: BETULA ALBA JUICE WHITE GEL
NDC: 76214-026 | Form: CREAM
Manufacturer: SKINFOOD CO., LTD.
Category: otc | Type: HUMAN OTC DRUG LABEL
Date: 20110923

ACTIVE INGREDIENTS: DIMETHICONE 2.72 g/50 g
INACTIVE INGREDIENTS: WATER; BETULA PUBESCENS RESIN; PROPYLENE GLYCOL; TRISILOXANE; GLYCERIN; NIACINAMIDE; BETAINE; BUTYLENE GLYCOL; MACADAMIA OIL; CYCLOMETHICONE 5; CETYL ETHYLHEXANOATE; C14-22 ALCOHOLS; METHYLPARABEN; PHENOXYETHANOL; PEG-40 STEARATE; C12-20 ALKYL GLUCOSIDE; PROPYLPARABEN; MEDIUM-CHAIN TRIGLYCERIDES; EDETATE DISODIUM; HONEY; HYALURONATE SODIUM; XANTHAN GUM

Drug Facts

Active ingredient: DIMETHICONE 5.44%

Inactive Ingredients:
WATER, BETULA ALBA JUICE, PROPYLENE GLYCOL, TRISILOXANE, BETA-GLUCAN, GLYCERIN, NIACINAMIDE, BETAINE, BUTYLENE GLYCOL, HYDROXYETHYL ACRYLATE/SODIUM ACRYLOYLDIMETHYL TAURATE COPOLYMER, ALGAE EXTRACT , DIISOSTEARYL MALATE, MACADAMIA TERNIFOLIA SEED OIL, CYCLOPENTASILOXANE, CETYL ETHYLHEXANOATE, TRIMETHYLSILOXYSILICATE, POLYGLYCERYL-3 METHYLGLUCOSE DISTEARATE, C14-22 ALCOHOLS, DIMETHICONE/VINYL DIMETHICONE CROSSPOLYMER, PEG-40 STEARATE, C12-20 ALKYL GLUCOSIDE, AMMONIUM ACRYLOYLDIMETHYLTAURATE/VP COPOLYMER, C12-14 PARETH-12, CAPRYLIC/CAPRIC TRIGLYCERIDE, DIACETYL BOLDINE, HONEY EXTRACT, HYDROLYZED VIOLA TRICOLOR EXTRACT, SODIUM HYALURONATE, XANTHAN GUM, DISODIUM EDTA, METHYLPARABEN, PROPYLPARABEN, PHENOXYETHANOL, FRAGRANCE

PURPOSE

Purpose: This combination of cosmetics / OTC Drug is used for your basic skin care and gives a benefit for Brightening care.

Warnings:
For external use only.
Avoid contact with eyes.
Discontinue use if signs of irritation appear.

Keep out of reach of children:
Keep out of reach of children.

Indication and usage:
Following emulsion, pour some on the palm of your hand and apply to skin gently.
Press down lightly until absorbed.

Dosage and administration:
Take appropriate amount according to your skin condition and apply every morning and night.